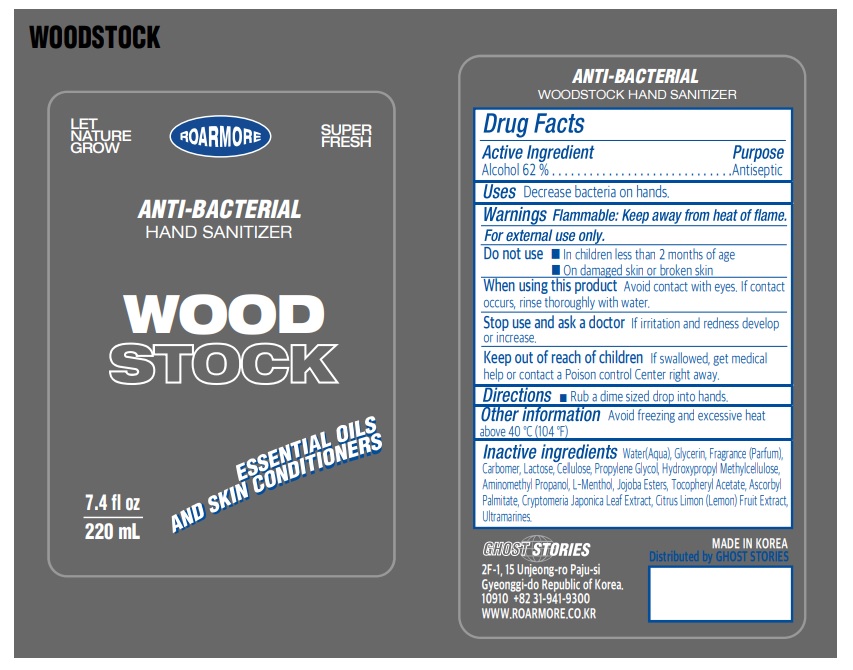 DRUG LABEL: ANTI-BACTERIAL WOODSTOCK HAND SANITIZER
NDC: 82697-220 | Form: GEL
Manufacturer: GHOST STORIES
Category: otc | Type: HUMAN OTC DRUG LABEL
Date: 20220420

ACTIVE INGREDIENTS: ALCOHOL 136.4 mL/220 mL
INACTIVE INGREDIENTS: LEMON; LACTOSE, UNSPECIFIED FORM; ULTRAMARINE BLUE; HYDROGENATED JOJOBA OIL, RANDOMIZED; HYPROMELLOSE, UNSPECIFIED; WATER; GLYCERIN; CARBOMER HOMOPOLYMER, UNSPECIFIED TYPE; AMINOMETHYLPROPANOL; LEVOMENTHOL; ALPHA-TOCOPHEROL ACETATE; ASCORBYL PALMITATE; POWDERED CELLULOSE; PROPYLENE GLYCOL; CRYPTOMERIA JAPONICA LEAF

82697-220-01 | ANTI-BACTERIAL WOODSTOCK HAND SANITIZER

Active ingredient

Alcohol 62%

Purpose

Antiseptic

Uses

Decrease bacteria on hands.

Warnings

Flammable: Keep away from heat of flame.

For external use only.

Do not use

- In children less than 2 months of age
- On damaged skin or broken skin

When using this product

Avoid contact with eyes. If contact occurs, rinse thoroughly with water.

Stop use and ask a doctor

If irritation and redness develop or increase.

Keep out of reach of children

If swallowed, get medical help or contact a Poison Control Cente right away.

Directions

- Rub a dime size drop into hands.

Other information

Avoid freezing and excessive heat above 40 °C (104 °F)

Inactive ingredients

Water(Aqua), Glycerin, Fragrance (Parfum), Carbomer, Lactose, Cellulose, Propylene Glycol, Hydroxypropyl Methylcellulose, Aminomethyl Propanol, L-Menthol, Jojoba Esters, Tocopheryl Acetate, Ascorbyl Palmitate, Cryptomeria Japonica Leaf Extract, Citrus Limon (Lemon) Fruit Extract, Ultramarines.